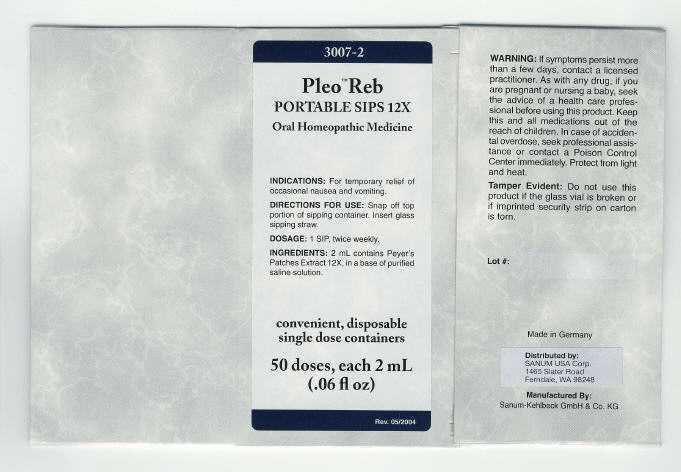 DRUG LABEL: Pleo Reb
NDC: 60681-3007 | Form: LIQUID
Manufacturer: Sanum Kehlbeck GmbH & Co. KG
Category: homeopathic | Type: HUMAN OTC DRUG LABEL
Date: 20100106

ACTIVE INGREDIENTS: sus scrofa small intestine mucosa lymph follicle 12 [hp_X]/2 mL
INACTIVE INGREDIENTS: water; sodium chloride

Pleo™ Reb
PORTABLE SIPS 12X

Oral Homeopathic Medicine

50 doses, each 2 mL
(.06 fl oz)

INDICATIONS

For temporary relief of occasional nausea and vomiting.

DIRECTIONS FOR USE

Snap off top portion of sipping container. Insert glass sipping straw.

DOSAGE

1 SIP, twice weekly

INGREDIENTS

2 mL contains Peyer's Patches Extract 12X, in a base of purified saline solution.

WARNING

If symptoms persist more than a few days, contact a licensed practitioner. As with any drug, if you are pregnant or nursing a baby, seek the advice of a health care professional before using this product.

KEEP OUT OF REACH OF CHILDREN

Keep this and all medications out of the reach of children. In case of accidental overdose, seek professional assistance or contact a Poison Control Center immediately.

STORAGE AND HANDLING

Protect from light and heat.

Tamper Evident

Do not use this product if the glass vial is broken or if imprinted security strip on carton is torn.

Made in Germany

Distributed by:
SANUM USA Corp.
1465 Slater Road
Ferndale, WA 98248

Manufactured By:
Sanum-Kehlbeck GmbH & Co. KG

Rev. 05/2004

PRINCIPAL DISPLAY PANEL - 2 mL Vial Carton

3007-2

Pleo™ Reb
PORTABLE SIPS 12X

Oral Homeopathic Medicine

INDICATIONS: For temporary relief of
occasional nausea and vomiting.

DIRECTIONS FOR USE: Snap off top
portion of sipping container. Insert glass
sipping straw.

DOSAGE: 1 SIP, twice weekly.

INGREDIENTS: 2 mL contains Peyer's
Patches Extract 12X, in a base of purified
saline solution.

convenient, disposable
single dose containers

50 doses, each 2 mL
(.06 fl oz)

Rev. 05/2004